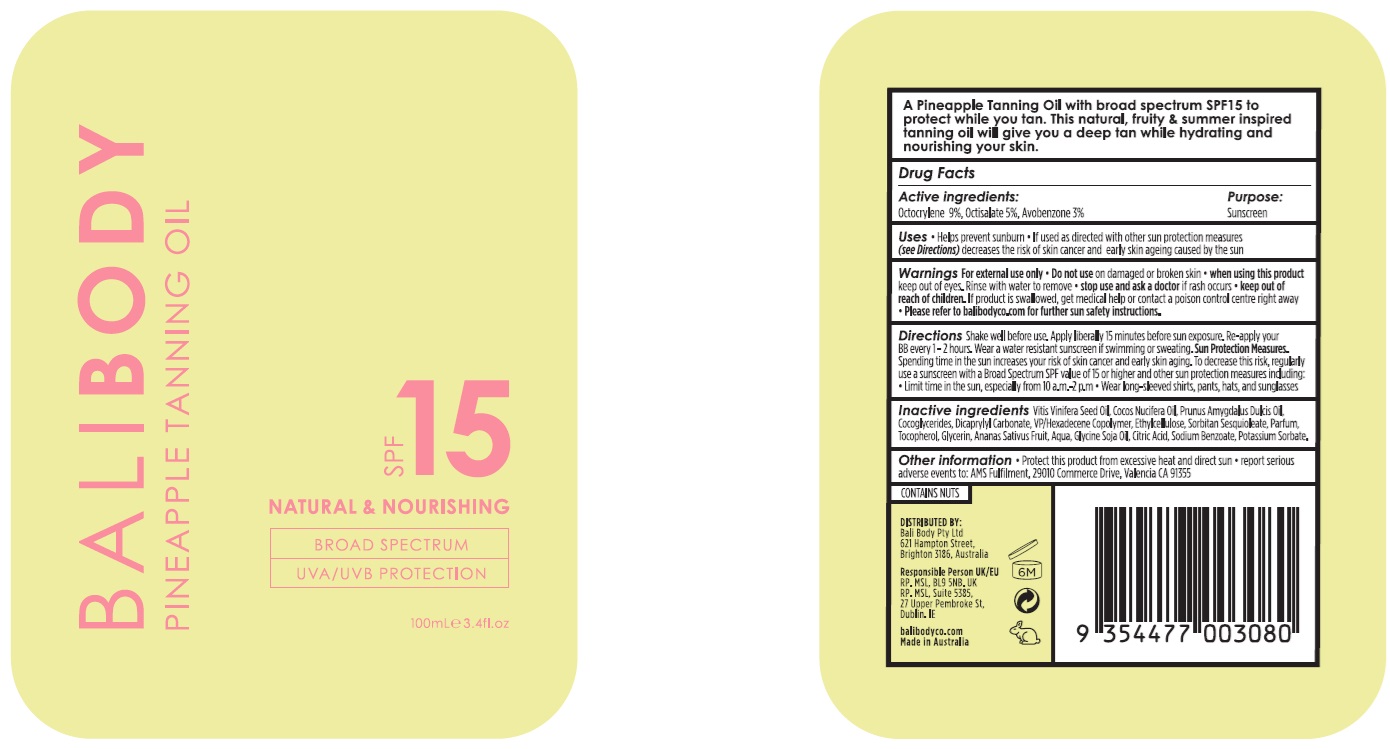 DRUG LABEL: Bali Body Pineapple Tanning Oil SPF15
NDC: 70630-0037 | Form: OIL
Manufacturer: Bali Body Pty Ltd
Category: otc | Type: HUMAN OTC DRUG LABEL
Date: 20241021

ACTIVE INGREDIENTS: OCTOCRYLENE 90 mg/1 mL; OCTISALATE 50 mg/1 mL; AVOBENZONE 30 mg/1 mL
INACTIVE INGREDIENTS: ETHYLCELLULOSE, UNSPECIFIED; GLYCERIN; VINYLPYRROLIDONE/HEXADECENE COPOLYMER; POTASSIUM SORBATE; CITRIC ACID MONOHYDRATE; GRAPE SEED OIL; ALMOND OIL; COCONUT OIL; DICAPRYLYL CARBONATE; PINEAPPLE; SOYBEAN OIL; TOCOPHEROL; WATER; SODIUM BENZOATE; COCO-GLYCERIDES; SORBITAN SESQUIOLEATE

Bali Body Pineapple Tanning Oil SPF15

Active ingredients:

Octocrylene 9%, Octisalate 5%, Avobenzone 3%

Purpose:

Sunscreen

Uses

- Helps prevent sunburn
- If used as directed with other sun protection measures (see Directions) decreases the risk of skin cancer and early skin ageing caused by the sun

Warnings

For external use only

Do not use

on damaged or broken skin

When using this product

keep out of eyes. Rinse with water to remove

Stop use and ask a doctor

if rash occurs

Keep out of reach of children.

If product is swallowed, get medical help or contact a poison control centre right away. Please refer to balibodyco.com for further sun safety instructions.

Directions

Shake well before use. Apply liberally 15 minutes before sun exposure. Re-apply your BB every 1-2 hours. Wear a water resistant suncreen if swimming or sweating. Sun Protection Measures. Spending time in the sun increases your risk of skin cancer and early skin aging. To decrease this risk, regularly use a sunscreen with a Broad Spectrum SPF value of 15 or higher and other sun protection measures including:

- Limit time in the sun, especially from 10 a.m.-2.p.m.
- Wear long-sleeved shirts, pants, hats, and sunglasses

Inactive ingredients

Vitis Vinifera Seed Oil, Cocos Nucifera Oil, Prunus Amygdalus Dulcis Oil, Cocoglycerides, Dicaprylyl Carbonate, VP/Hexadecene Copolymer, Ethylcellulose, Sorbitan Sesquioleate, Parfum, Tocopherol, Glycerin, Ananas Sativus Fruit, Aqua, Glycine Soja Oil, Citric Acid, Sodium Benzoate, Potassium Sorbate.

Other information

- Protect this product from excessive heat and direct sun
- report serious adverse events to: AMS Fulfilment, 29010 Commerce Drive, Valencia, CA 91355